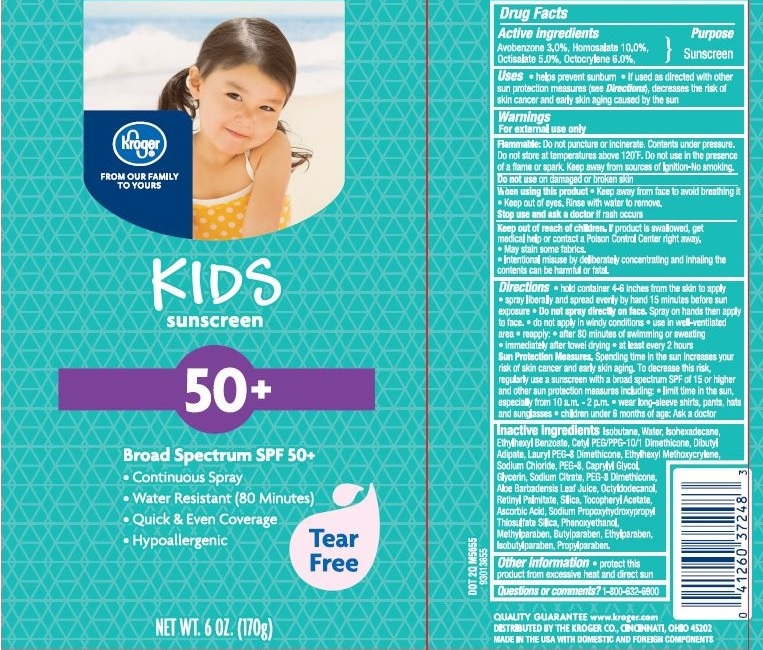 DRUG LABEL: KROGER KIDS TEAR FREE  SPF50 
                        
NDC: 30142-655 | Form: SPRAY
Manufacturer: Kroger Company
Category: otc | Type: HUMAN OTC DRUG LABEL
Date: 20160105

ACTIVE INGREDIENTS: AVOBENZONE 3 g/100 g; HOMOSALATE 10 g/100 g; OCTISALATE 5 g/100 g; OCTOCRYLENE 6 g/100 g
INACTIVE INGREDIENTS: ISOBUTANE; ISOHEXADECANE; 2-ETHYLHEXYL BENZOATE; DIBUTYL ADIPATE; WATER; ETHYLHEXYL METHOXYCRYLENE; SODIUM CHLORIDE; POLYETHYLENE GLYCOL 400; CAPRYLYL GLYCOL; GLYCERIN; SODIUM CITRATE, UNSPECIFIED FORM; PEG-8 DIMETHICONE; ALOE VERA LEAF; OCTYLDODECANOL; VITAMIN A PALMITATE; SILICON DIOXIDE; .ALPHA.-TOCOPHEROL ACETATE; ASCORBIC ACID; SODIUM PROPOXYHYDROXYPROPYL THIOSULFATE SILICA; PHENOXYETHANOL; METHYLPARABEN; BUTYLPARABEN; ETHYLPARABEN; ISOBUTYLPARABEN; PROPYLPARABEN

Drug Facts

Active Ingredients

Avobenzone 3.0%, Homosalate 10.0%, Octisalate 5.0%, Octocrylene 6.0%

Purpose

Sunscreen

Uses

- helps prevent sunburn
- if used as directed with other sun protection measures (see Directions), decreases the risk of skin cancer and early skin aging caused by the sun

Warnings

For external use only.

Flammable:Do not puncture or incinerate. Contents under pressure. Do not store at temperatures above 120^0F. Do not use in the presence of a flame or spark. Keep away from sources of ignition-No smoking.

Do not use

on damaged or broken skin.

When using this product

- Keep away from face to avoid breathing it.
- Keep out of eyes. Rinse with water to remove.

Stop use and ask a doctor

if rash occurs.

Keep out of reach of children

If product is swallowed, get medical help or contact a Poison Control Center right away,

- May stain some fabrics.
- Intentional misuse by deliberately concentrating and inhaling the contents can be harmful or fatal.

Directions

- hold container 4-6 inches from the skin to apply
- spray liberally and spread evenly by hand 15 minutes before sun exposure
- Do not spray directly on face.Spray on hands then apply on face.
- do not apply in windy condition
- use in well-ventilated area
- reapply: after 80 minutes of swimming or sweating
- immediately after towel drying
- at least every 2 hours

Sun Protection Measures, Spending time in the sun increases your risk of skin cancer and early skin aging. To decrease this risk, regularly use a sunscreen with broad spectrum SPF of 15 or higher and other sun protection measures including

- limit time in the sun especially from 10.00 a.m. - 2.00 p.m.
- wear long-sleeve shirts, pants, hats and sunglasses
- children under 6 months of age: Ask a doctor

Inactive Ingredients

Isobutane, Water, Isohexadecane, Ethylhexyl Benzoate, Cetyl PEG/PPG-10/1 Dimethicone, Dibutyl Adipate, Lauryl PEG-8 Dimethicone, Ethylhexyl Methoxycrylene, Sodium Chloride, PEG-8, Caprylyl Glycol, Glycerin, Sodium Citrate, PEG-8 Dimethicone, Aloe Barbadensis Leaf Juice, Octyldodecanol, Retinyl Palmitate, Silica, Tocopheryl Acetate, Ascorbic Acid, Sodium Propoxyhydroxypropyl Thiosulfate Silica, Phenoxyethanol, Methylparaben, Butylparaben, Ethylparaben, Isobutylparaben, Propylparaben.

Other Information

- protect this product from excessive heat and direct sun

Questions or Comments?

Call 1-800-632-6900

Principal Display Panel

NDC 30142-655-34

Kroger

FROM OUR FAMILY

TO YOURS

KIDS

sunscreen

50+

Broad Spectrum SPF 50+

- Continuous Spray
- Water Resistant (80 Minutes)
- Quick and Even Coverage
- Hypoallergenic

Tear Free

NET WT. 6 OZ. (170g)